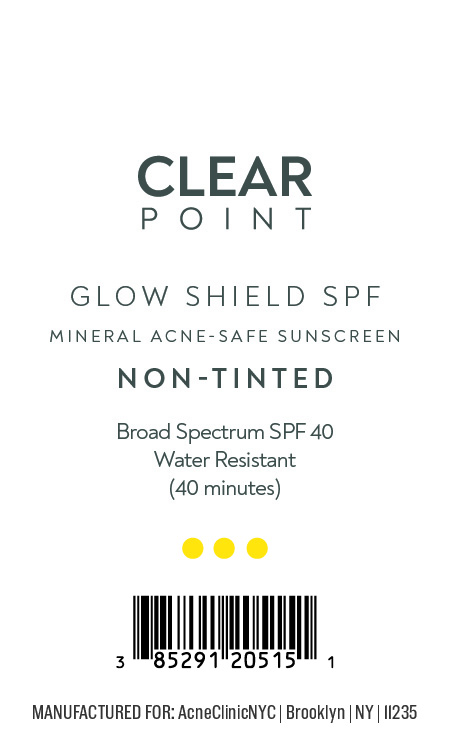 DRUG LABEL: GLOW SHIELD SPF
NDC: 85291-205 | Form: CREAM
Manufacturer: ACNE SOLUTIONS NYC INC
Category: otc | Type: HUMAN OTC DRUG LABEL
Date: 20251208

ACTIVE INGREDIENTS: ZINC OXIDE 200 mg/1 g
INACTIVE INGREDIENTS: PEG-10 DIMETHICONE (600 CST); POLYSORBATE 20; DIMETHICONOL (2000 CST); DIMETHICONE/VINYL DIMETHICONE CROSSPOLYMER (SOFT PARTICLE); HYDROGEN DIMETHICONE (20 CST); ALPHA-TOCOPHEROL ACETATE; WATER; GLYCERIN; TRIETHANOLAMINE; TRIETHOXYCAPRYLYLSILANE; DIMETHICONE; PEG-30 DIPOLYHYDROXYSTEARATE; CYCLOHEXASILOXANE; STEARYL DIMETHICONE (400 MPA.S AT 50C); EDETATE DISODIUM ANHYDROUS; CYCLOPENTASILOXANE; CAPRYLHYDROXAMIC ACID; POLYHYDROXYSTEARIC ACID (2300 MW); TETRAHEXYLDECYL ASCORBATE; CETYL PEG/PPG-10/1 DIMETHICONE (HLB 4); DIMETHICONE CROSSPOLYMER; MICROCRYSTALLINE WAX; CAPRYLYL GLYCOL; POLYGLYCERYL-4 ISOSTEARATE; C12-15 ALKYL BENZOATE; SODIUM CHLORIDE

Active Ingredient:

Zinc Oxide 20%

Purpose:

Sunscreen

Warning:

For external use only. Keep out of the reach of children.

Warning:

For external use only. Keep out of reach of children.

Directions:

Apply liberally 15 minutes before sun exposure.

INACTIVE INGREDIENT

C12-15 Alkyl Benzoate, Caprylhydroxamic Acid, Caprylyl Glycol, Cetyl PEG/PPG-10/1 Dimethicone, Cyclohexasiloxane, Cyclopentasiloxane, Dimethicone, Dimethicone Crosspolymer, Dimethicone/Vinyl Dimethicone Crosspolymer, Dimethiconol, Disodium EDTA, Glycerin, Hydrogen Dimethicone, Microcrystalline Wax, PEG-10 Dimethicone, PEG-30 Dipolyhydroxystearate, Polyglyceryl-4 Isostearate, Polyhydroxystearic Acid, Polysorbate 20, Sodium Chloride, Stearyl Dimethicone, Tetrahexyldecyl Ascorbate, Tocopheryl Acetate, Triethanolamine, Triethoxycaprylylsilane, Water

Warning:

Keep out of reach of children